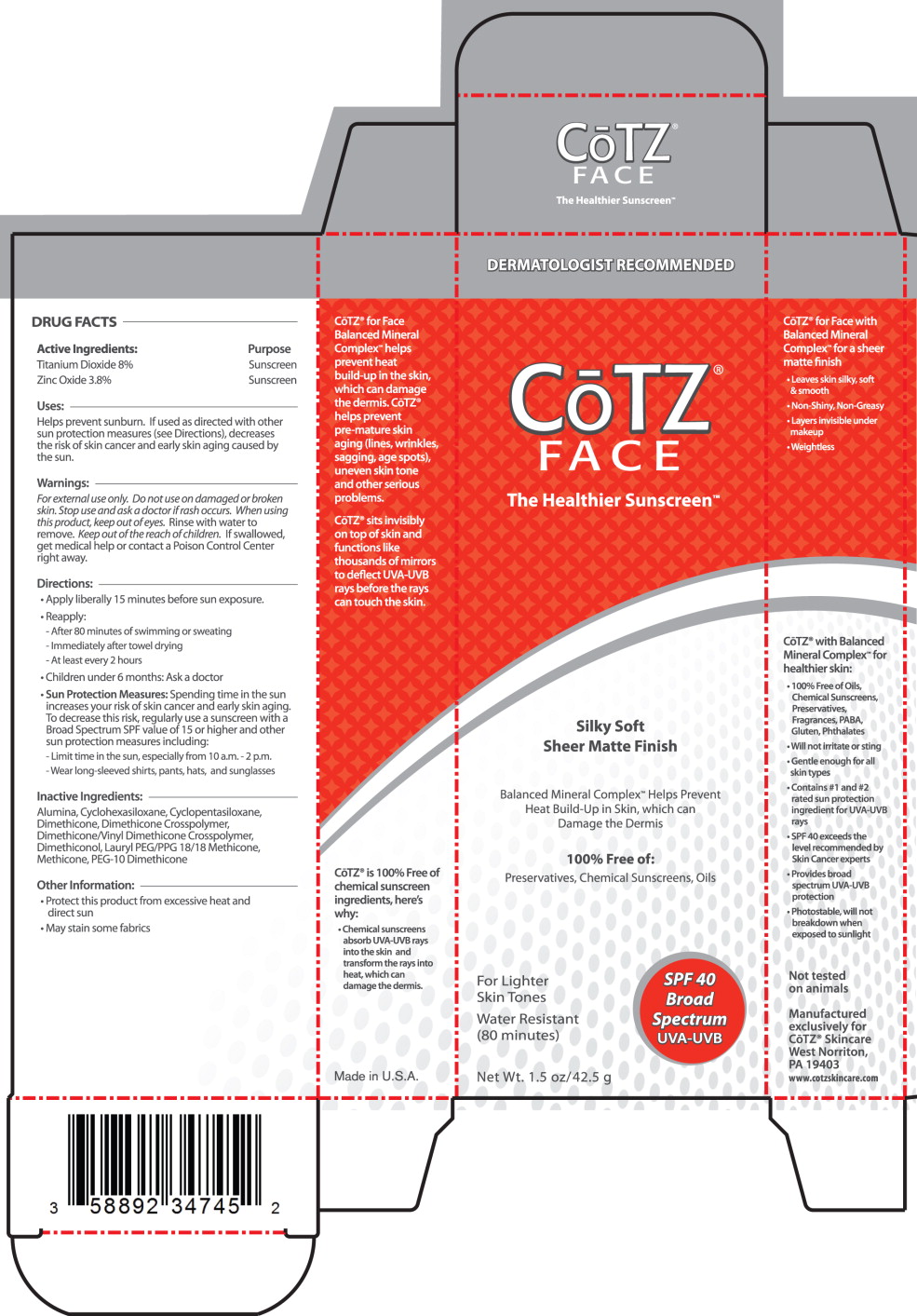 DRUG LABEL: Cotz Face (For Lighter Skin Tones) SPF 40 
NDC: 58892-347 | Form: CREAM
Manufacturer: Fallien Cosmeceuticals, LTD.
Category: otc | Type: HUMAN OTC DRUG LABEL
Date: 20130103

ACTIVE INGREDIENTS: Titanium Dioxide 80 mg/1 g; Zinc Oxide 38 mg/1 g
INACTIVE INGREDIENTS: Aluminum Oxide; Cyclomethicone 6; Cyclomethicone 5; Dimethicone 20; Dimethicone/Diene Dimethicone Crosspolymer; Dimethiconol (100000 cst); Lauryl PEG/PPG-18/18 Methicone; Methicone (20 cst); PEG-10 Dimethicone (600 cst)

DRUG FACTS

Active Ingredients:

Titanium Dioxide 8%

Zinc Oxide 3.8%

Purpose

Sunscreen

Sunscreen

Uses:

Helps prevent sunburn. If used as directed with other sun protection measures (see Directions), decreases the risk of skin cancer and early skin aging caused by the sun.

Warnings:

For external use only.

Do not use on damaged or broken skin.

Stop use and ask a doctor if rash occurs.

When using this product, keep out of eyes. Rinse with water to remove.

KEEP OUT OF REACH OF CHILDREN

Keep out of the reach of children. If swallowed, get medical help or contact a Poison Control Center right away.

Directions:

- Apply liberally 15 minutes before sun exposure.
- Reapply:
  - After 80 minutes of swimming or sweating
  - Immediately after towel drying
  - At least every 2 hours
- Children under 6 months: Ask a doctor
- Sun Protection Measures: Spending time in the sun increases your risk of skin cancer and early skin aging. To decrease this risk, regularly use a sunscreen with a Broad Spectrum SPF value of 15 or higher and other sun protection measures including:
  - Limit time in the sun, especially from 10 a.m. - 2 p.m.
  - Wear long-sleeved shirts, pants, hats, and sunglasses

Inactive Ingredients:

Alumina, Cyclohexasiloxane, Cydopentasiloxane, Dimethicone, Dimethicone Crosspolymer, Dimethicone/Vinyl Dimethicone Crosspolymer, Dimethiconol, Lauryl PEG/PPG 18/18 Methicone, Methicone, PEG-10 Dimethicone

Other Information:

- Protect this product from excessive heat and direct sun
- May stain some fabrics

Principal Display Panel – 1.5 oz Carton Label

DERMATOLOGIST RECOMMENDED

CoTZ®

FACE

The Healthier Sunscreen TM

Silky Soft
Sheer Matte Finish

Balanced Mineral ComplexTM Helps Prevent
Heat Build-Up in Skin, which can
Damage the Dermis

100% Free of:

Preservatives, Chemical Sunscreens, Oils

SPF 40

Broad

Spectrum

UVA-UVB

For Lighter
Skin Tones

Water Resistant
(80 minutes)

Net Wt. 1.5 oz/42.5 g